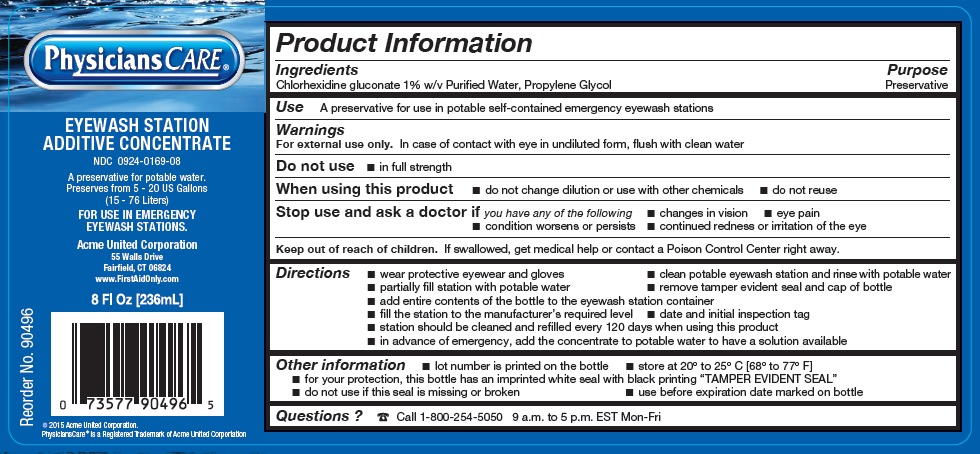 DRUG LABEL: PhysiciansCare Eyewash Station Additive Concentrate
NDC: 0924-0169 | Form: SOLUTION
Manufacturer: Acme United Corporation
Category: otc | Type: HUMAN OTC DRUG LABEL
Date: 20191104

ACTIVE INGREDIENTS: PROPYLENE GLYCOL 280 kg/2800 L; CHLORHEXIDINE GLUCONATE 145.6 kg/2800 L
INACTIVE INGREDIENTS: WATER 2374.4 L/2800 L

PhysiciansCare Eyewash Station Additive Concentrate

ACTIVE INGREDIENT

Ingredients

Chlorhexidine gluconate 1% w/v Purified Water, Propylene Glycol

Purpose

Preservative

Use

A preservative for use in potable self-contained emergency eyewash stations

Warnings

For external use only. In case of contact with eye in undiluted form, flush with clean water

Do not use

- in full strength

When using this product

- do not change dilution or use with other chemicals
- do not reuse

Stop use and ask a doctor ifyou have any of the following

- changes in vision
- eye pain
- condition worsens or persists
- continued redness or irritations of the eye

Keep out of reach of children. If swallowed, get medical help or contact a Poison Control Center right away.

Directions

- wear protective eyewear and gloves
- clean potable eyewash station and rinse with potable water
- partially fill station with potable water
- remove tamper evident seal and cap of bottle
- add entire contents of the bottle to the eyewash station container
- fill the station to the manufacturer's required level
- date and initial inspection tag
- station should be cleaned and refilled every 120 days when using this product
- in advance of emergency, add the concentrate to potable water to have solution available

Other information

- lot number is printed on the bottle
- store at 20º to 25º C [68º to 77º F]
- for your protection, this bottle has an imprinted white seal with black printing "TAMPER EVIDENT SEAL"
- do not use if this seal is missing or broken
- use before expiration date marked on bottle

QUESTIONS

Questions? Call 1-800-254-5050 9 a.m. to 5 p.m. EST Mon-Fri

Inactive Ingredients

Water

PRINCIPAL DISPLAY PANEL - 236 mL Bottle Label

EYEWASH STATION ADDITIVE CONCENTRATE

NDC 0924-0169-08

A preservative for potable water.

Preserves from 5 - 20 US Gallons

(15 - 76 Liters)

FOR USE IN EMERGENCY

EYEWASH STATIONS

Acme United Corporation

55 Walls Drive

Fairfield, CT 06824

www.FirstAidOnly.com

8 Fl Oz [236mL]